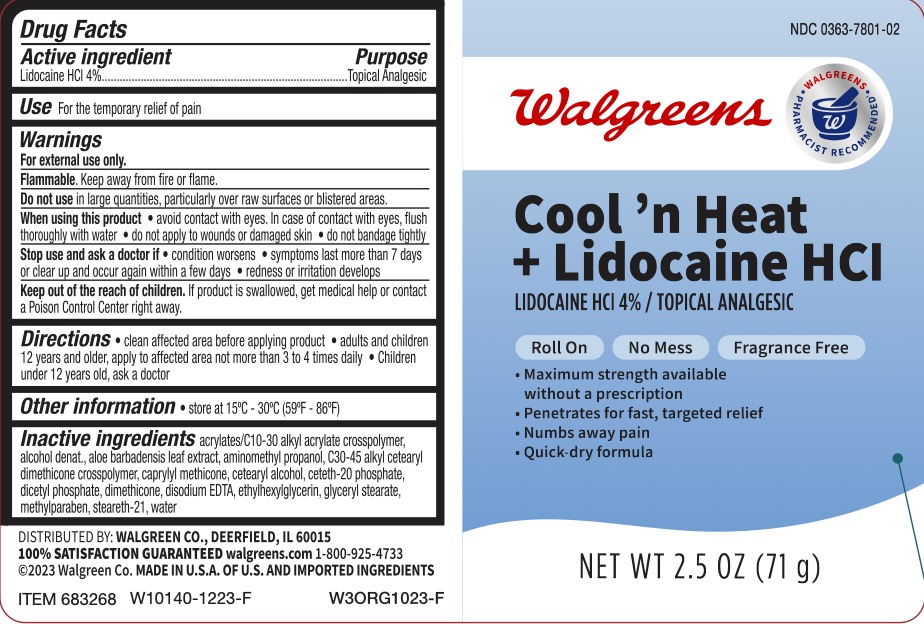 DRUG LABEL: Walgreens Cool n Heat Lidocaine
NDC: 0363-7801 | Form: GEL
Manufacturer: Walgreens Co
Category: otc | Type: HUMAN OTC DRUG LABEL
Date: 20231227

ACTIVE INGREDIENTS: LIDOCAINE HYDROCHLORIDE 4 g/100 g
INACTIVE INGREDIENTS: WATER; DIMETHICONE 200; EDETATE DISODIUM; ALOE VERA LEAF; C30-45 ALKYL CETEARYL DIMETHICONE CROSSPOLYMER; CETETH-20 PHOSPHATE; METHYLPARABEN; ACRYLATES/C10-30 ALKYL ACRYLATE CROSSPOLYMER (60000 MPA.S); AMINOMETHYLPROPANOL; ALCOHOL; CAPRYLYL TRISILOXANE; CETOSTEARYL ALCOHOL; DIHEXADECYL PHOSPHATE; GLYCERYL MONOSTEARATE; STEARETH-21; ETHYLHEXYLGLYCERIN

Walgreens Cool n' Heat

ACTIVE INGREDIENT

Lidocaine HCl 4%

PURPOSE

Topical analgesic

INDICATIONS AND USAGE

For the temporary relief of pain.

WARNINGS

For external use only.

Flammable.Keep away from fire or flame.

Do not use inlarge quantities, particularly over raw surfaces or blistered areas.

When using this product

- avoid contact with eyes. In case of contact with eyes, flush thoroughly with water
- do not apply to wounds or damaged skin
- do not bandage tightly

Stop use and ask a doctor if

- condition worsens
- symptoms last more than 7 days or clear up and occur again with a few days
- redness or irritation develops

KEEP OUT OF REACH OF CHILDREN

If product is swallowed, get medical help or contact a Poison Control Center right away.

DOSAGE AND ADMINISTRATION

Clean affected area before applying product. Adults and children 12 years and older, apply to affected area not more than 3 to 4 times daily. Children under 12 years old, ask a doctor.

INACTIVE INGREDIENT

Acrylates/C10-30 alkyl acrylate crosspolymer, alcohol denat., aloe barbadensis leaf extract, aminomethyl propanol, C30-45 alkyl cetearyl dimethicone crosspolymer, caprylyl methicone, cetearyl alcohol, ceteth-20 phosphate, dicetyl phosphate, dimethicone, disodium EDTA, ethylhexylglycerin, glyceryl stearate, methylparaben, steareth-21 water.